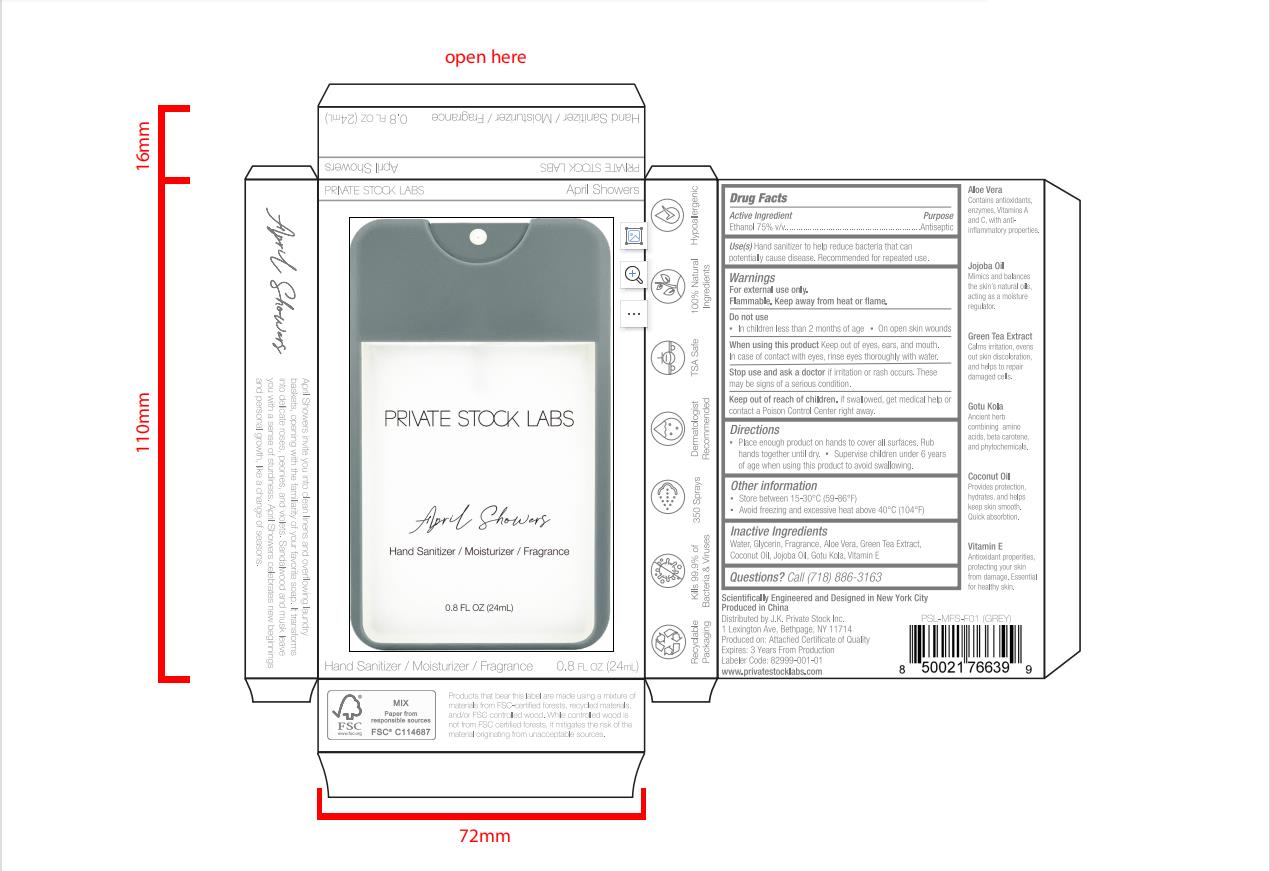 DRUG LABEL: Hand Sanitizer
NDC: 77975-011 | Form: LIQUID
Manufacturer: Guangzhou Tingcai Cosmetic Co., Ltd.
Category: otc | Type: HUMAN OTC DRUG LABEL
Date: 20230306

ACTIVE INGREDIENTS: ALCOHOL 75 mL/100 mL
INACTIVE INGREDIENTS: ALOE VERA WHOLE; GREEN TEA LEAF; WATER; GLYCERIN; ALOE VERA LEAF; COCONUT OIL; JOJOBA OIL; CENTELLA ASIATICA LEAF; .ALPHA.-TOCOPHEROL

77975-011
Hand Sanitizer

Active Ingredient(s)

Ethanol 75%

Purpose

Antiseptic

Use

Hand sanitizer to help reduce bacteria that potentially can causedisease. For use when soap and water are not avallableFor external use only. Flammable. Keep away from fire or flame.

Warnings

For external use only.

Flammable. Keep away from heat or flame.

Do not use

In children less than 2 months of age.

On open skin wounds

When using this product Keep out of eyes, ears, and mouth. In case of contact with eyes, rinse eyes throughly with water.

Stop use and ask a doctor if irritation or rash occurs. These may be sians of a serious condition.

KEEP OUT OF REACH OF CHILDREN

Keep out of reach of chlldren. If swallowed. get medical help or contact a Polson Control center right away.

Directions

Place enough product on hands to cover all surfaces. Rub hands together until dry.

Supervise children under 6 years of age When using this product to avoid swallowing.

Other information

Store between 15-30C (59-86F).

Avold freezing andexcessive heat above 40C(104F).

Inactive ingredients

Water, Glycerin, Fragrance, Aloe Vera, Green Tea Extract, Coconut Oil, Jojoba Oil, Gotu Kola, Vitamin E